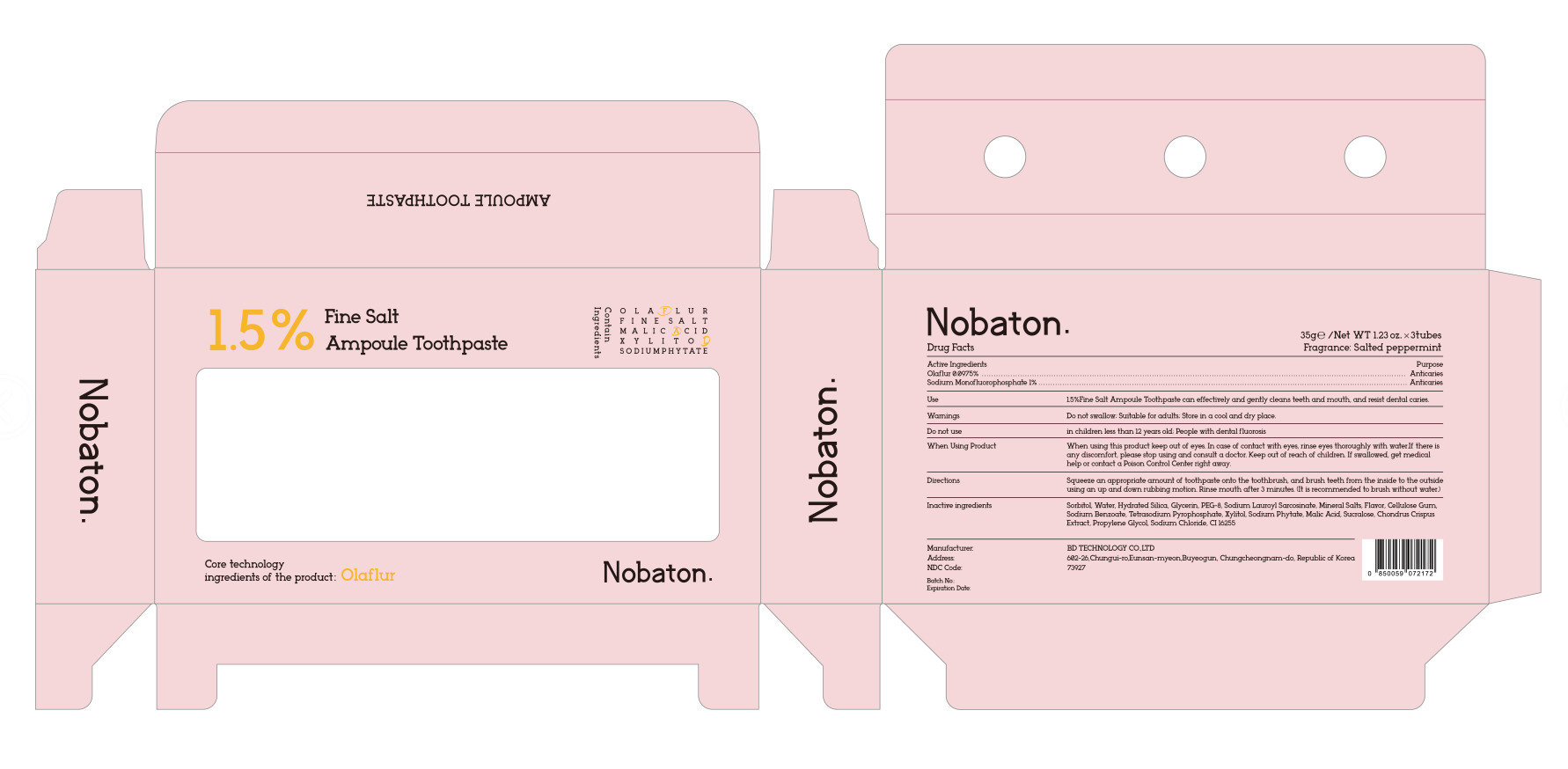 DRUG LABEL: Nobaton 1.5%Fine Salt ampoule
NDC: 73927-0009 | Form: OINTMENT
Manufacturer: BD TECHNOLOGY CO.,LTD
Category: otc | Type: HUMAN OTC DRUG LABEL
Date: 20250420

ACTIVE INGREDIENTS: SODIUM MONOFLUOROPHOSPHATE 1 g/100 g; OLAFLUR 0.0975 g/100 g
INACTIVE INGREDIENTS: SODIUM BENZOATE; TETRASODIUM PYROPHOSPHATE; MALIC ACID; XYLITOL; CHONDRUS CRISPUS CARRAGEENAN; SUCRALOSE; CELLULOSE GUM; SODIUM CHLORIDE; CI 16255; SORBITOL; WATER; HYDRATED SILICA; PEG-8; GLYCERIN; SODIUM LAUROYL SARCOSINATE; FLAVOR SPICE MINT N&A110589; SODIUM PHYTATE; CHROMITE; PROPYLENE GLYCOL

73927-0009
Nobaton 1.5%Fine Salt ampoule toothpaste

Active Ingredient(s)

OLAFLUR 0.0975%

SODIUM MONOFLUOROPHOSPHATE 1%

Purpose

Anticaries

Use

15%Fine Salt Ampoule Toothpaste can effectively and gently cleans teeth and mouth, and resist dental caries.

Warnings

Do not swallow; Suitable for adults: Store in a cool and dry place.

Do not use

in children less than 12 years old; People with dental fluorosis

When using this product keep out of eyes. In case of contact with eyes, rinse eyes thoroughly with waterIf there is
any discomfort, please stop using and consult a doctor. Keep out of reach of children. If swallowed, get medical
help or contact a Poison Control Center right away.

STOP USE

In case of contact with eyes, rinse eyes thoroughly with waterIf there

Keep out of reach of children.

Directions

Squeeze an appropriate amount of toothpaste onto the toothbrush, and brush teeth from the inside to the outside
using an up and down rubbing motion. Rinse mouth after 3 minutes. (It is recommended to brush without water.)

Other information

No

Inactive ingredients

Sorbitol, Water, Hydrated Silica, Glycerin, PEG-8, Sodium Lauroyl Sarcosinate, Mineral Salts, Flavor, Cellulose Gum,
Sodium Benzoate, Tetrasodium Pyrophosphate, Xylitol Sodium Phytate, Malic Acid, Sucralose, Chondrus Crispus
Extract, Propylene Glycol, Sodium Chloride, CI 16255